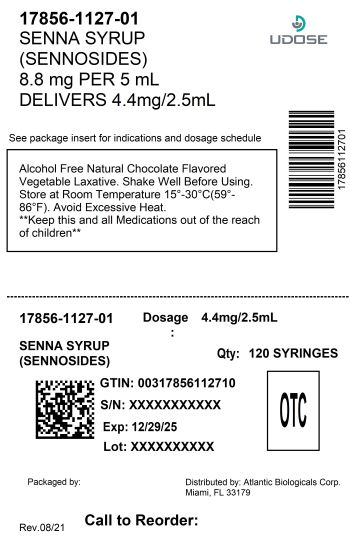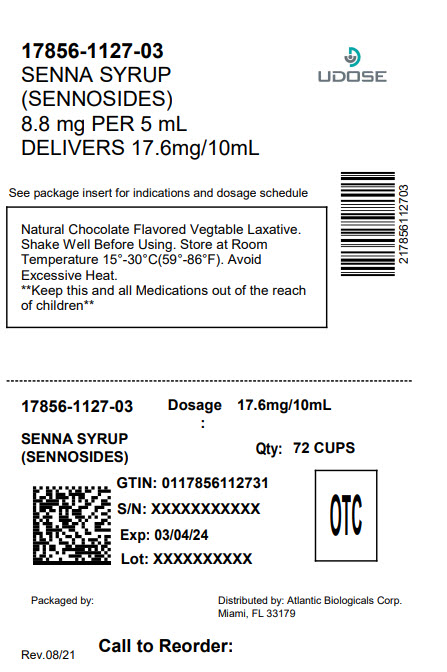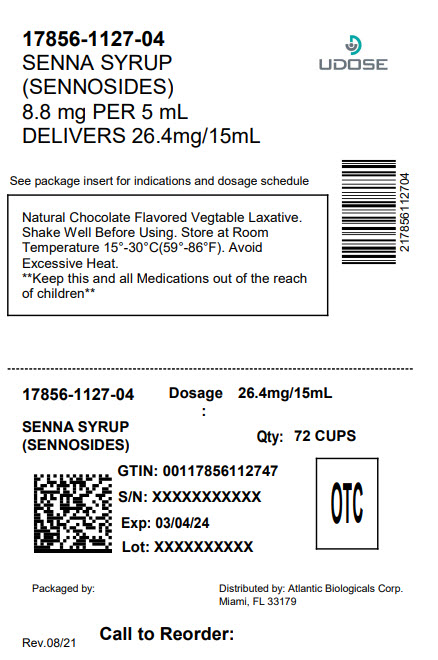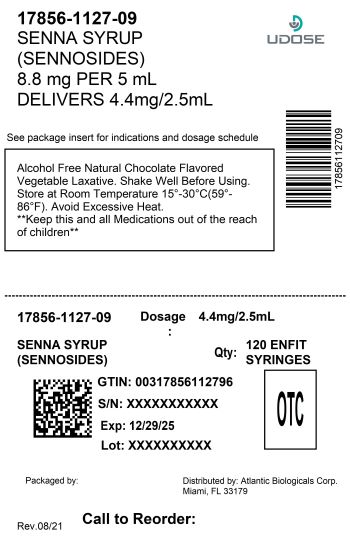 DRUG LABEL: OneLAX SENNA
NDC: 17856-1127 | Form: SYRUP
Manufacturer: ATLANTIC BIOLOGICALS CORP.
Category: otc | Type: HUMAN OTC DRUG LABEL
Date: 20251229

ACTIVE INGREDIENTS: SENNOSIDES A AND B 417.12 mg/237 mL
INACTIVE INGREDIENTS: METHYLPARABEN; PROPYLENE GLYCOL; PROPYLPARABEN; WATER; SUCROSE

OneLAX SENNA SYRUP
Natural Vegitable Lexative
Natural Choclate Flavor

Active Ingredient

Active ingredient(in each teaspoonful) Purpose
Sennosides 8.8 mg …………………………................Laxative

Uses

relieves occasional constipation (irregularity), generally causes bowel movement in 6 to 12 hours

Warnings

ask a doctor before use if you have • stomach pain • nausea • vomiting • noticed a sudden change in bowel movements that continues over a period of 2 weeks

Do not use laxative products for longer than 1 week unless directed by a doctor

Ask a doctor or pharmacist before use if

you are taking any other drug. Take this product two more hours before or after other drugs. Laxatives may affect how other drugs work.

Stop use and ask a doctor if

you have rectal bleeding or fail to have bowel movement after use of laxative. This may indicate a serious condition.

If pregnant or breast-feeding,

ask a health professional before use.

Keep out of reach of children

In case of overdose, get medical help or contact a Poison Control Center right away.

Directions

take preferably at bedtime or as directed by a doctor. Shake Well Before Using.

age | starting dose | maximum dosage
Adults and children 12 yeart and older | 2-3 teaspoons once a day | 3 teaspoons twice a day
Children 6 years to under 12 yeart | 1 - 11/2teaspoons once a day | 11/2teaspoons twice a day
Children 2 years to under 6 yeart | l/2-3/4teaspoon once a day | 3/4 teaspoon twice a day
Children under 2 years | ask a doctor | ask a doctor

Other Information

- Avoid accessive heat. Store at room temperature 15°-30°C (59°-86°F)

Inactive Ingredients

flavor choclate, mythylparaben, propylene glycol, propylparaben, purified water and sucrose

KEEP OUT OF REACH OF CHILDREN SECTION

In case of accidental overdose, get medical help or contact a Poison Control Center immediately

Questions?

To Report Adverse Drug Event Call 1(877) 225-6999

DISTRIBUTED BY:

ATLANTIC BIOLOGICALS CORP.

MIAMI, FL 33179